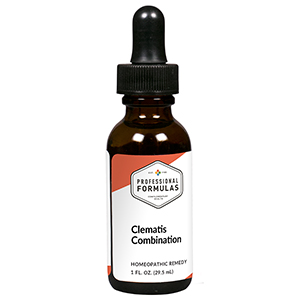 DRUG LABEL: Clematis Combination
NDC: 63083-9219 | Form: LIQUID
Manufacturer: Professional Complementary Health Formulas
Category: homeopathic | Type: HUMAN OTC DRUG LABEL
Date: 20190815

ACTIVE INGREDIENTS: BETULA PUBESCENS WHOLE 2 [hp_X]/29.5 mL; CALTHA PALUSTRIS WHOLE 3 [hp_X]/29.5 mL; GALIUM APARINE WHOLE 3 [hp_X]/29.5 mL; SEDUM ACRE WHOLE 3 [hp_X]/29.5 mL; THUJA OCCIDENTALIS LEAF 3 [hp_X]/29.5 mL; URTICA URENS WHOLE 3 [hp_X]/29.5 mL; CLEMATIS RECTA FLOWERING TOP 4 [hp_X]/29.5 mL; HEDERA HELIX FLOWERING TWIG 4 [hp_X]/29.5 mL; JUNIPERUS COMMUNIS VAR. SAXATILIS WHOLE 4 [hp_X]/29.5 mL; ONONIS REPENS WHOLE 4 [hp_X]/29.5 mL; QUILLAJA SAPONARIA WOOD 4 [hp_X]/29.5 mL; SEMPERVIVUM TECTORUM LEAF 4 [hp_X]/29.5 mL; ECHINACEA ANGUSTIFOLIA WHOLE 5 [hp_X]/29.5 mL; CALCIUM FLUORIDE 6 [hp_X]/29.5 mL; NITRIC ACID 6 [hp_X]/29.5 mL; SILVER 8 [hp_X]/29.5 mL; PHOSPHORUS 8 [hp_X]/29.5 mL; APIS MELLIFERA 12 [hp_X]/29.5 mL; RANCID BEEF 12 [hp_X]/29.5 mL
INACTIVE INGREDIENTS: ALCOHOL; WATER

R219

ACTIVE INGREDIENTS

Betula alba 2X
Caltha palustris 3X
Galium aparine 3X
Sedum acre 3X
Thuja occidentalis 3X
Urtica urens 3X
Clematis erecta 4X
Hedera helix 4X
Juniperus communis 4X
Ononis spinosa 4X
Quillaja saponaria 4X
Sempervivum tectorum 4X
Echinacea angustifolia 5X
Calcarea fluorica 6X
Nitricum acidum 6X
Argentum metallicum 8X
Phosphorus 8X
Apis mellifica 12X
Pyrogenium 12X

QUESTIONS

Professional Formulas

PO Box 2034 Lake Oswego, OR 97035

INDICATIONS

For the temporary relief of minor aches, swelling, pain, or tingling of the joints, muscles, or extremities.*

PURPOSE

*Claims based on traditional homeopathic practice, not accepted medical evidence. Not FDA evaluated.

WARNINGS

In case of overdose, get medical help or contact a poison control center right away.

Keep out of the reach of children.

PREGNANCY OR BREAST FEEDING

If pregnant or breastfeeding, ask a healthcare professional before use.

DIRECTIONS

Place drops under tongue 30 minutes before/after meals. Adults and children 12 years and over: Take 10 drops up to 3 times per day. Consult a physician for use in children under 12 years of age.

OTHER INFORMATION

Tamper resistant. If seal is broken, do not use. After opening, close container tightly and store at room temperature away from heat.

INACTIVE INGREDIENTS

40% ethanol, purified water.

LABEL

Est 1985

Professional Formulas

Complementary Health

Clematis Combination

Homeopathic Remedy

1 FL. OZ. (29.5 mL)